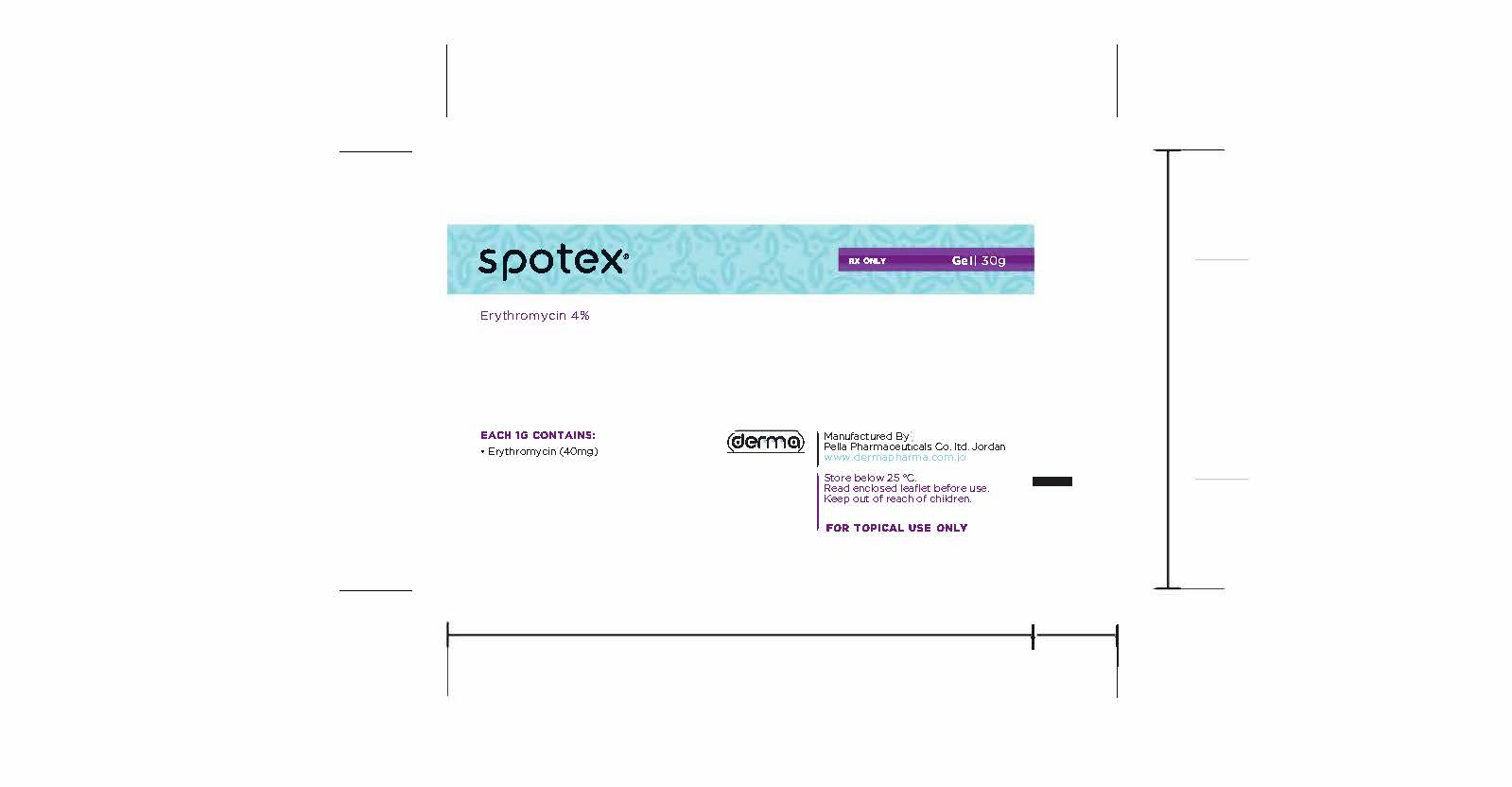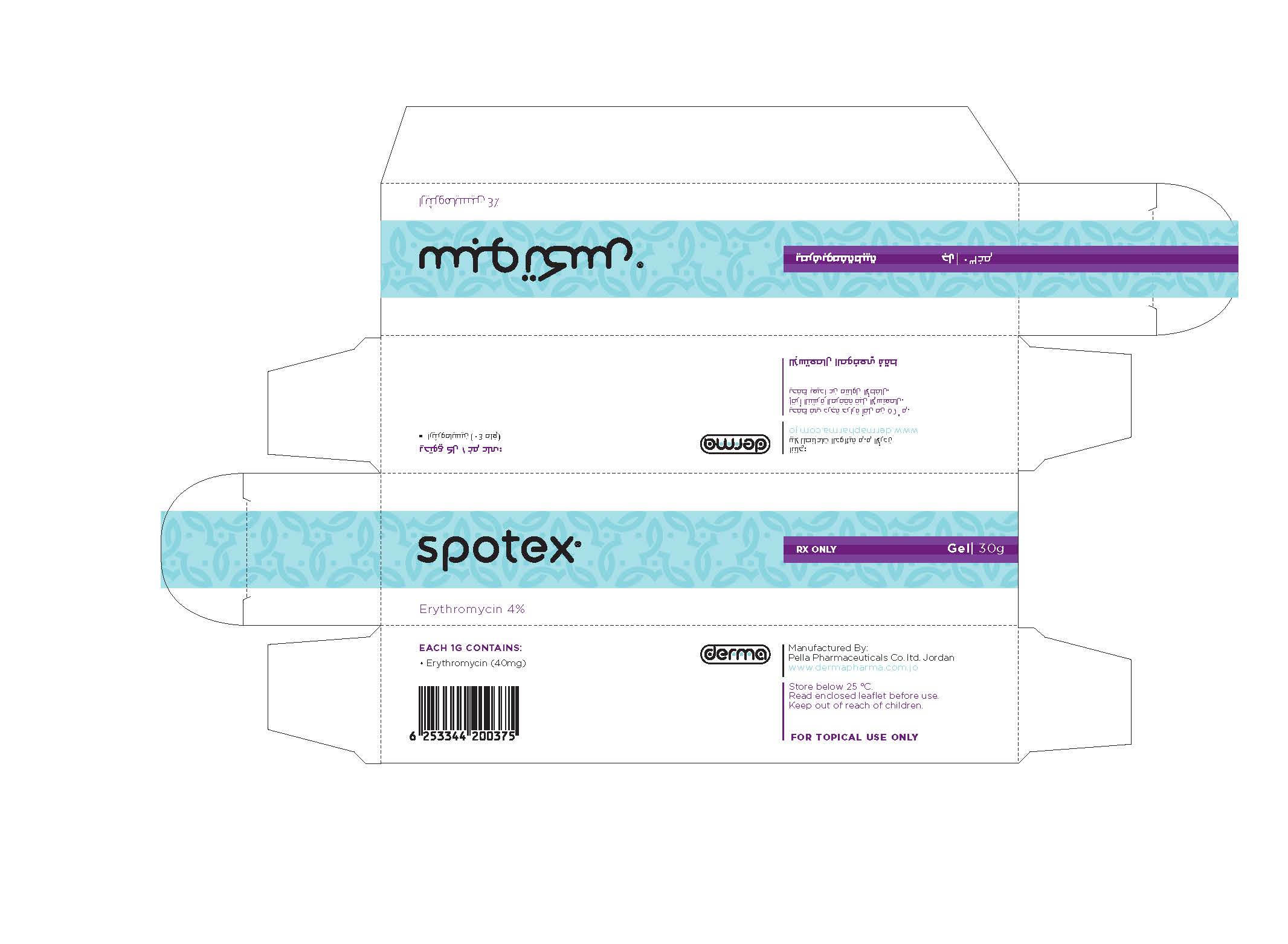 DRUG LABEL: Spotex
NDC: 82160-126 | Form: GEL
Manufacturer: Pella Pharmaceuticals Co. Ltd
Category: prescription | Type: HUMAN PRESCRIPTION DRUG LABEL
Date: 20241231

ACTIVE INGREDIENTS: ERYTHROMYCIN 1200 mg/30 g

Spotex

Composition

Each 1 g contains: Erythromycin base 40 mg.
Excipients: Ethanol 99.9%, Hydroxypropyl cellulose, Butylated hydroxytoluene.

Properties

Erythromycin which belongs to a class of chemicals called macrolide antibiotics; exerts its antibacterial action by binding to the 50S ribosomal subunit of susceptible bacteria and suppressing protein synthesis. Erythromycin is usually bacteriostatic but may be bactericidal in high concentrations or against highly susceptible organisms.

Indications

Spotex is indicated for the treatment of Acne Vulgaris, Acne appears as blackheads and whiteheads which people often refer to as pimples or spots. Spotex attacks the bacteria that are one of the main causes of acne. The name of these bacteria is Propionibacterium acnes

Contraindications

Spotex is contraindicated if you are allergic (hypersensitive) to Erythromycin or any of the other ingredients of Spotex.
An allergic reaction may include a rash or itching.

Precautions

If you use Spotex on your face don t get it in your eyes, nose/nostrils, mouth, or on your lips. If you do, wash the area with large amount of warm water. And do not use Spotex on areas where you have cuts or scrapes.
Excessive exposure to sunlight or ultraviolet rays (sun lamps) should be avoided during treatment with Spotex because the additional irradiation may lead to a more intense action.
If sunburn occurs, it is advisable to interrupt therapy until the severe erythema and peeling subside. Patients whose occupations require considerable exposure to the sun should exercise particular caution.

Pregnancy

Ask your doctor or pharmacist for advice before taking any medicine.

Lactation

Do not apply Spotex on your chest if you are breast feeding.
Ask your doctor or pharmacist for advice before taking any medicine.

Drug Interactions

Do not use Spotex with any other acne products that are used on the skin unless your doctor or pharmacist has told you that you can.
While you are using Spotex, do not use skin cleansers that remove dead skin (these are called exfoliants), medicated soaps or cosmetics containing alcohol. These could make your skin irritated or dry.
Please tell your doctor or pharmacist if you are taking or have recently taken any other medicines, including medicines obtained without a prescription.

Warnings

Topical gels and creams are intended for external use only and should be kept away from eyes, nose, mouth, and other mucous membranes because of its irritant effect. Do not apply to eyelids or to the skin at the corners of the eyes and mouth. Avoid the angles of the nose and nasolabial fold (if treatment in these areas; is necessary, apply very sparingly). Topical use may induce severe local erythema and peeling at the site of application. If the degree of local irritation warrants, patients should be directed to use the medication less frequently, discontinue use temporarily or discontinue use altogether.

Dosage and Administration

Use Spotex once in the morning and once in the evening, unless your doctor or pharmacist has told you otherwise.
Wash the affected areas with water or with a mild cleanser, and then thoroughly dry the affected areas and gently apply on a thin film of Spotex using the tips of your fingers. Don't forget to wash your hands afterwards.

The alcohol quickly evaporates and erythrornycin penetrates into your skin without leaving an unpleasant film, after you have used Spotex; screw the cap tightly on the tube.

How long you will have to use Spotex will depend on how quickly your acne improves. You may well use Spotex Gel for one month and then a lower strength product for one more month. Your doctor will decide which strength to prescribe for you.
It is recommended to use sunscreens over treated areas before sun exposure.

Overdosage

Do not put too much Spotex on your skin. You will not get rid of the acne any quicker. If you put on too much, your skin may become irritated and red. Some peeling or discomfort could also occur. If any of these happen, use Spotex once a day in the evening until they have gone. Then apply Spotex twice a day as you did previously. If the effects continue or are causing you a lot of discomfort, stop using the product and ask your doctor or pharmacist for advice.
In the rare event that you accidentally swallow any of this product, seek medical advice.

Side Effects

Like all medicines Spotex can cause side effects, although not everybody gets them. These might include dryness, itching, redness, peeling or oiliness. You might feel a stinging or burning sensation when you put it on your skin. Usually the effects are not serious and happen at the start of treatment. More often than not, they go away as you continue to use the gel.
If any of the side effects gets serious, or if you notice any side effects not listed in this leaflet, please tell your doctor or pharmacist.

Storage

Store below 25 °C.

How supplied

30 g packs.

THIS IS A MEDICAMENT

- Medicament is a product which affects your health and its consumption contrary to instructions is dangerous for you.
- Strictly follow the doctor's prescription, the method of use and the instruction of the pharmacist who sold the medicament.
- The doctor and the pharmacist are experts in medicine, its benefits and risks.
- Do not by yourself interrupt the period of treatment prescribed for you.
- Do not repeat the same prescription without consulting your doctor.
- Keep medicament out of reach of children